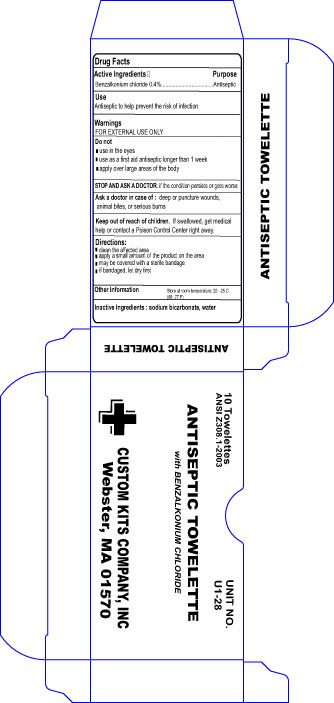 DRUG LABEL: Antiseptic Towelettes
NDC: 68183-120 | Form: CLOTH
Manufacturer: Custom Kits Company Inc
Category: otc | Type: HUMAN OTC DRUG LABEL
Date: 20171227

ACTIVE INGREDIENTS: BENZALKONIUM CHLORIDE 1.3 mg/1 mL
INACTIVE INGREDIENTS: SODIUM BICARBONATE; WATER

Antiseptic Towelette

Active Ingredients

Benzalkonium chloride .4%

Purpose Section

Antiseptic

Uses

Antiseptic to help prevent the risk of infection

Warning

For External Use Only

Do Not

use in the eyes

use as a first aid antiseptic longer than 1 week

apply over large areas of the body

Stop Use

if the condition persists or gets worse

Ask a doctor in case of

deep or puncture wounds, animal bites, or serious burns

Keep out of reach of children section

If swallowed, get medical help or contact a poison control center right away.

Directions

Clean the affected area

apply a small amount of the product on the area

may be covered with a sterile bandage

if bandaged let dry first

Other information

store at room temperature 20-25C (68-77 F)

Inactive Ingredients

Sodium bicarbonate, water